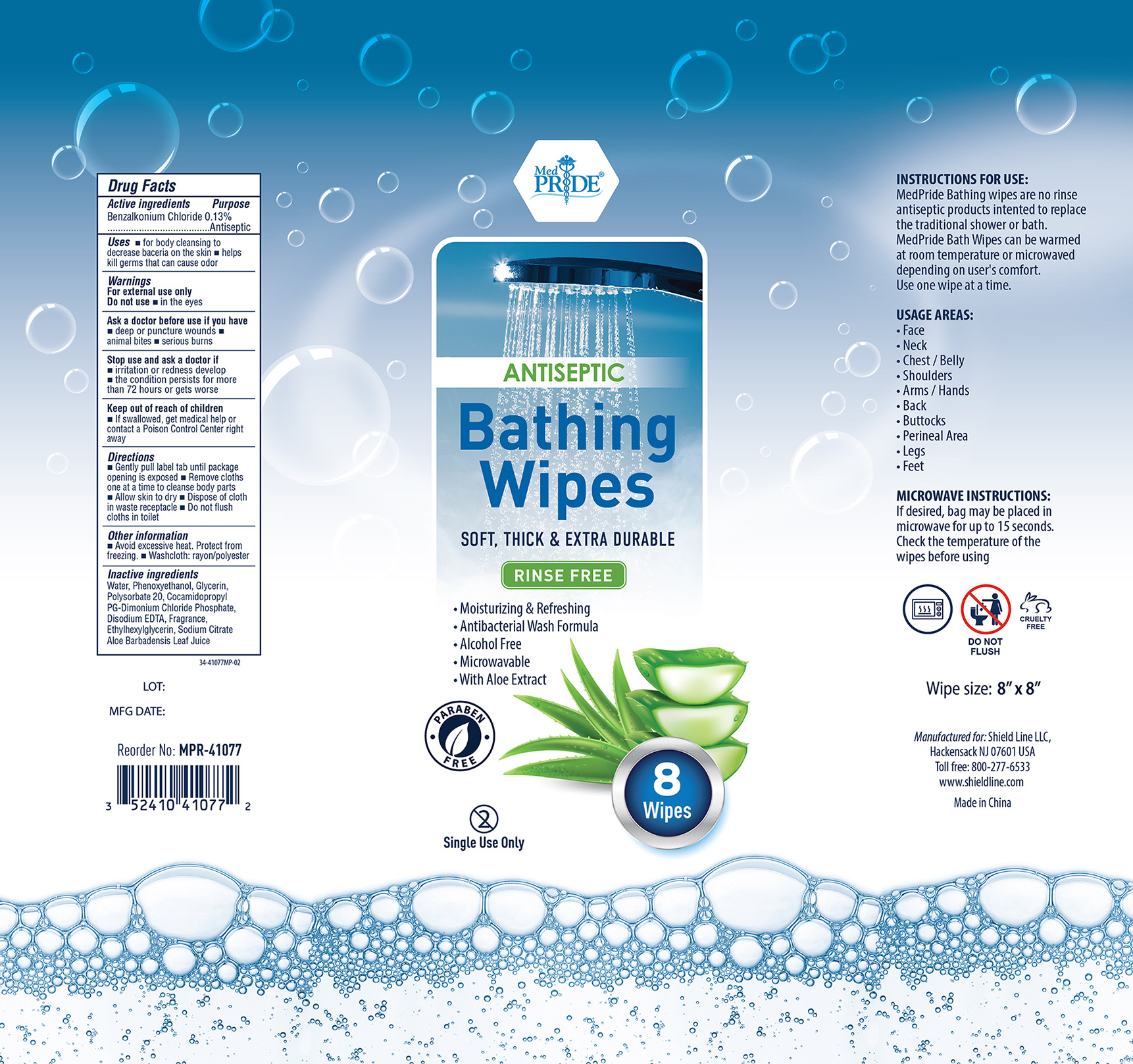 DRUG LABEL: MedPride Bath Wipes
NDC: 52410-4107 | Form: CLOTH
Manufacturer: Shield Line LLC
Category: otc | Type: HUMAN OTC DRUG LABEL
Date: 20250815

ACTIVE INGREDIENTS: BENZALKONIUM CHLORIDE 0.13 g/100 g
INACTIVE INGREDIENTS: GLYCERIN; PHENOXYETHANOL; DEHYDROACETIC ACID; COCAMIDOPROPYL PG-DIMONIUM CHLORIDE PHOSPHATE; BENZOIC ACID; ETHYLHEXYLGLYCERIN; POLYSORBATE 20; ALOE VERA LEAF; SODIUM CITRATE; EDETATE DISODIUM; WATER

MedPride Bath Wipes MPR-41077

Active ingredient

Benzalkonium chloride 0.13%

Purpose

Antiseptic

Uses

- for body cleansing to decrease bacteria on the skin
- helps kill germs that can cause odor

Warnings

For external use only

Do not use

- in the eyes

Ask a doctor before use if you have

- deep or puncture wounds
- animal bites
- serious burns

Stop use and ask a doctor if

- irritation and redness develop
- the condition persists for more than 72 hours or gets worse

Keep out of reach of children.

If swallowed get medical help or contact a Poison Control Center right away.

Directions

- gently pull label tab until package opening is exposed
- remove cloths one at a time to cleanse body parts
- allow skin to dry
- dispose of cloth in waste receptacle
- do not flush cloths in toilet

Other information

- avoid excessive heat, protect from freezing
- washcloth: rayon/polyester

Inactive ingredients

water, Phenoxyethanol, Glycerine, Polysorbate 20, Cocamidopropyl PG-Dimonium Chloride Phosphate, Disodium EDTA, Fragrance, Ethylhexylglycerin, Sodium Citrate, Aloe Barbadensis Leaf Juice